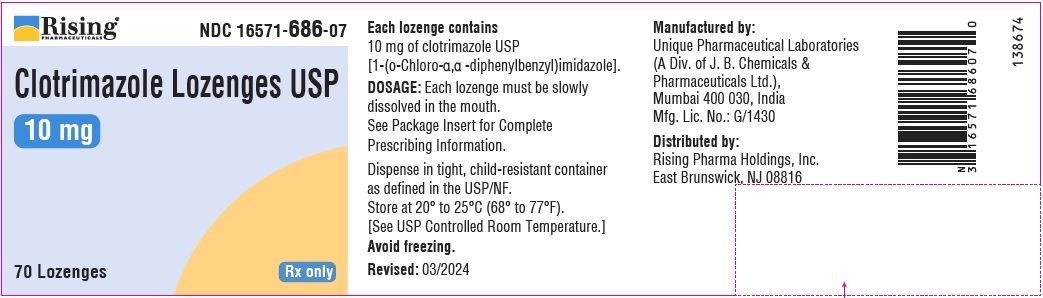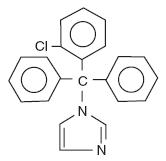 DRUG LABEL: CLOTRIMAZOLE
NDC: 16571-686 | Form: LOZENGE
Manufacturer: Rising Pharma Holdings, Inc.
Category: prescription | Type: HUMAN PRESCRIPTION DRUG LABEL
Date: 20250327

ACTIVE INGREDIENTS: CLOTRIMAZOLE 10 mg/1 1
INACTIVE INGREDIENTS: DEXTRATES; MICROCRYSTALLINE CELLULOSE; CROSCARMELLOSE SODIUM; POVIDONE K30; MAGNESIUM STEARATE

Clotrimazole Lozenges USP 10 mg

FOR TOPICAL ORAL ADMINISTRATION

Rx only

DESCRIPTION

Each Clotrimazole lozenge USP contains 10 mg clotrimazole USP [1-(o-chloro-α,α-diphenylbenzyl) imidazole], a synthetic antifungal agent, for topical use in the mouth.

Structural Formula:

Chemical Formula: C22 H17 ClN2

The lozenge dosage form is a large, slowly dissolving lozenge containing 10 mg of clotrimazole USP dispersed in croscarmellose sodium, dextrates, magnesium stearate, microcrystalline cellulose and povidone.

CLINICAL PHARMACOLOGY

Clotrimazole is a broad-spectrum antifungal agent that inhibits the growth of pathogenic yeasts by altering the permeability of cell membranes. The action of clotrimazole is fungistatic at concentrations of drug up to 20 mcg/mL and may be fungicidal in vitro against Candida albicans and other species of the genus Candida at higher concentrations. No single-step or multiple-step resistance to clotrimazole has developed during successive passages of Candida albicans in the laboratory; however, individual organism tolerance has been observed during successive passages in the laboratory. Such in vitro tolerance has resolved once the organism has been removed from the antifungal environment.

After oral administration of a 10 mg clotrimazole lozenge to healthy volunteers, concentrations sufficient to inhibit most species of Candida persist in saliva for up to three hours following the approximately 30 minutes needed for a lozenge to dissolve. The long term persistence of drug in saliva appears to be related to the slow release of clotrimazole from the oral mucosa to which the drug is apparently bound. Repetitive dosing at three hour intervals maintains salivary levels above the minimum inhibitory concentrations of most strains of Candida; however, the relationship between in vitro susceptibility of pathogenic fungi to clotrimazole and prophylaxis or cure of infections in humans has not been established.

In another study, the mean serum concentrations were 4.98 ± 3.7 and 3.23 ± 1.4 nanograms/mL of clotrimazole at 30 and 60 minutes, respectively, after administration as a lozenge.

INDICATIONS AND USAGE

Clotrimazole Lozenges are indicated for the local treatment of oropharyngeal candidiasis. The diagnosis should be confirmed by a KOH smear and/or culture prior to treatment.

Clotrimazole Lozenges are also indicated prophylactically to reduce the incidence of oropharyngeal candidiasis in patients immunocompromised by conditions that include chemotherapy, radiotherapy, or steroid therapy utilized in the treatment of leukemia, solid tumors, or renal transplantation. There are no data from adequate and well-controlled trials to establish the safety and efficacy of this product for prophylactic use in patients immunocompromised by etiologies other than those listed in the previous sentence. (See DOSAGE AND ADMINISTRATION.)

CONTRAINDICATIONS

Clotrimazole Lozenges are contraindicated in patients who are hypersensitive to any of its components.

WARNING

Clotrimazole Lozenges are not indicated for the treatment of systemic mycoses including systemic candidiasis.

PRECAUTIONS

Abnormal liver function tests have been reported in patients treated with clotrimazole lozenges; elevated SGOT levels were reported in about 15% of patients in the clinical trials. In most cases the elevations were minimal and it was often impossible to distinguish effects of clotrimazole from those of other therapy and the underlying disease (malignancy in most cases). Periodic assessment of hepatic function is advisable particularly in patients with pre-existing hepatic impairment.

Since patients must be instructed to allow each lozenge to dissolve slowly in the mouth in order to achieve maximum effect of the medication, they must be of such an age and physical and/or mental condition to comprehend such instructions.

Carcinogenesis

An 18 month dosing study with clotrimazole in rats has not revealed any carcinogenic effect.

Use In Pregnancy

Pregnancy Category C:

Clotrimazole has been shown to be embryotoxic in rats and mice when given in doses 100 times the adult human dose (in mg/kg), possibly secondary to maternal toxicity. The drug was not teratogenic in mice, rabbits, and rats when given in doses up to 200, 180, and 100 times the human dose.

Clotrimazole given orally to mice from nine weeks before mating through weaning at a dose 120 times the human dose was associated with impairment of mating, decreased number of viable young, and decreased survival to weaning. No effects were observed at 60 times the human dose. When the drug was given to rats during a similar time period at 50 times the human dose, there was a slight decrease in the number of pups per litter and decreased pup viability.

There are no adequate and well controlled studies in pregnant women. Clotrimazole lozenges should be used during pregnancy only if the potential benefit justifies the potential risk to the fetus.

Pediatric Use

Safety and effectiveness of clotrimazole in children below the age of 3 years have not been established; therefore, its use in such patients is not recommended.

The safety and efficacy of the prophylactic use of clotrimazole lozenges in children have not been established.

Geriatric Use

Clinical studies of clotrimazole did not include sufficient numbers of subjects aged 65 and over to determine whether they respond differently from younger subjects. Other reported clinical experience has not identified differences in responses between the elderly and younger patients.

ADVERSE REACTIONS

Abnormal liver function tests have been reported in patients treated with clotrimazole lozenges; elevated SGOT levels were reported in about 15% of patients in the clinical trials (See PRECAUTIONS).

Nausea, vomiting, unpleasant mouth sensations and pruritus have also been reported with the use of the lozenge.

To report SUSPECTED ADVERSE REACTIONS, contact Rising Pharma Holdings, Inc. at 1-844-874-7464 or FDA at 1-800-FDA-1088 or www.fda.gov/medwatch

OVERDOSAGE

No data available.

DRUG ABUSE AND DEPENDENCE

No data available.

DOSAGE AND ADMINISTRATION

Clotrimazole Lozenges are administered only as a lozenge that must be slowly dissolved in the mouth. The recommended dose is one lozenge five times a day for fourteen consecutive days. Only limited data are available on the safety and effectiveness of the clotrimazole lozenge after prolonged administration; therefore, therapy should be limited to short term use, if possible.

For prophylaxis to reduce the incidence of oropharyngeal candidiasis in patients immunocompromised by conditions that include chemotherapy, radiotherapy, or steroid therapy utilized in the treatment of leukemia, solid tumors, or renal transplantation, the recommended dose is one lozenge three times daily for the duration of chemotherapy or until steroids are reduced to maintenance levels.

HOW SUPPLIED

Clotrimazole Lozenges USP

10 mg lozenge is supplied as white to off white, round, flat face beveled edge lozenge debossed with “227” on one side and “P” on the other side.

NDC 16571-686-07: Bottle of 70 Lozenges with child-resistant closure.

NDC 16571-686-14: Bottle of 140 Lozenges with child-resistant closure.

STORAGE AND HANDLING

Store at 20° to 25°C (68° to 77°F). [See USP Controlled Room Temperature.]

Avoid freezing.

Manufactured by:

Unique Pharmaceutical Laboratories

(A Div. of J.B. Chemicals & Pharmaceuticals Ltd.)

Mumbai 400 030, India

Distributed by:

Rising Pharma Holdings, Inc.

East Brunswick, NJ 08816

141367

Revised: 03/2025

PRINCIPAL DISPLAY PANEL

NDC 16571-686-07

Clotrimazole Lozenges USP

10 mg

70 Lozenges